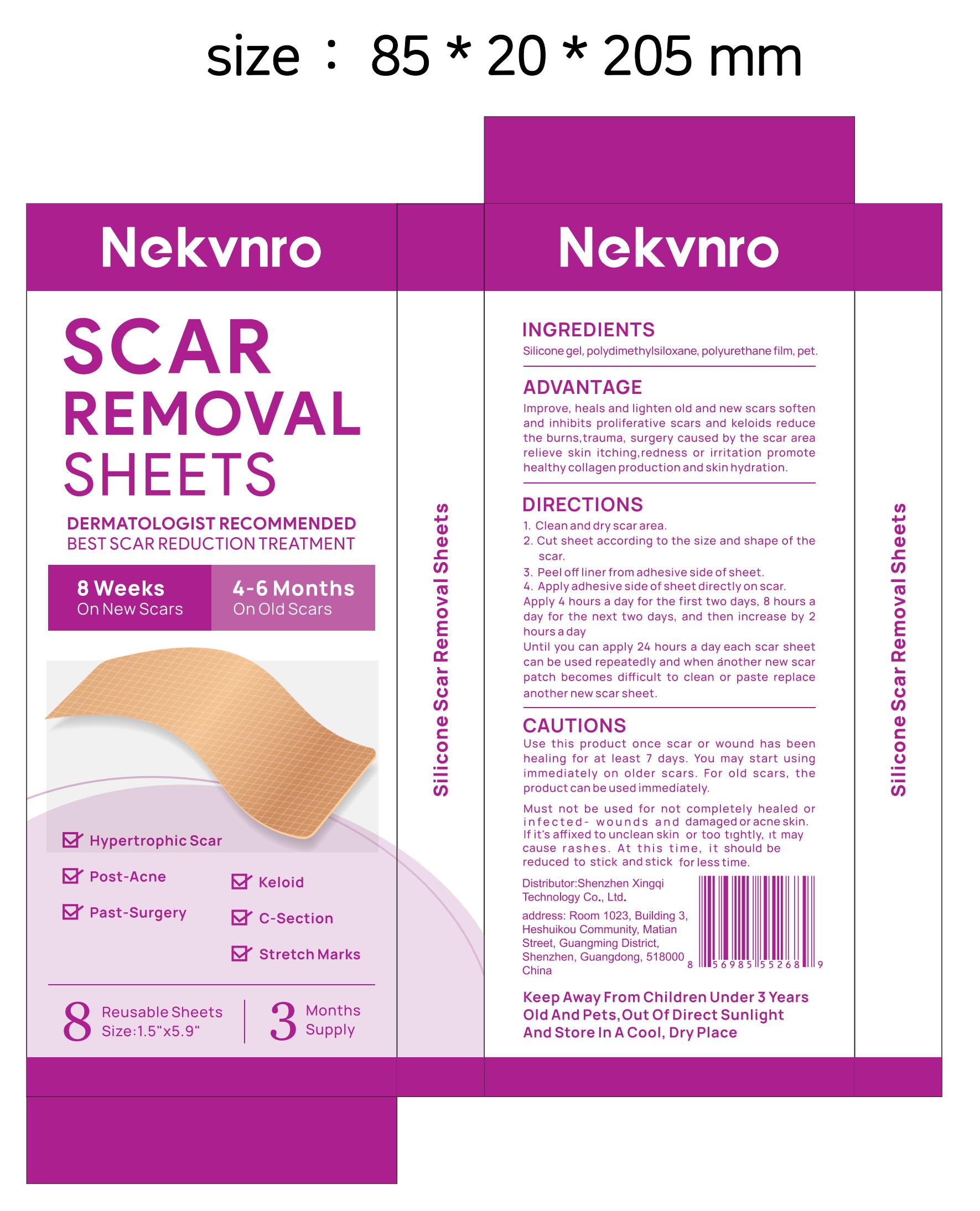 DRUG LABEL: Nekvnro SCAR REMOVAL SHEETS
NDC: 84613-054 | Form: PATCH
Manufacturer: Shenzhen Xingqi Technology Co., Ltd.
Category: otc | Type: HUMAN OTC DRUG LABEL
Date: 20240808

ACTIVE INGREDIENTS: DIMETHICONE 1 g/100 g
INACTIVE INGREDIENTS: POLYETHYLENE TEREPHTHALATE (INTRINSIC VISCOSITY 0.40-0.70); POLYURETHANE-39; CYCLOMETHICONE

ACTIVE INGREDIENT

DIMETHICONE 5%

PURPOSE

SCAR REMOVAL

uses

1. Clean and dry scar area.
2. Cut sheet according to the size and shape of the
scar.
3. Peel off liner from adhesive side of sheet.
4. Apply adhesive side of sheet directly on scar.
Apply 4 hours a day for the first two days, 8 hours a
day for the next two days, and then increase by 2
hours a day
Until you can apply 24 hours a day each scar sheet
can be used repeatedly and when ánother new scar
patch becomes difficult to clean or paste replace
another new scar sheet.

Warning

Use this product once scar or wound has been
healing for at least 7 days. You may start using
immediately on older scars. For old scars, the
product can be usedimmediately.
Must not be used for not completely healed or
infected- wounds and damaged or acne skin.
If it's affixed to unclean skin or too tightly, it may
cause rashes. At this time, it should be
reduced to stick and stick for less time.

Dosage and administration

For external use only.

Do not use

Discontinue use if any irritation or adverse reaction occurs

When using section

Use this product once scar or wound has been
healing for at least 7 days. You may start using
immediately on older scars. For old scars, the
product can be usedimmediately.
Must not be used for not completely healed or
infected- wounds and damaged or acne skin.
If it's affixed to unclean skin or too tightly, rt may
cause rashes. At this time,it should be
reduced to stick and stick for less time.

stop use

Use this product once scar or wound has been
healing for at least 7 days. You may start using
immediately on older scars. For old scars, the
product can be usedimmediately.
Must not be used for not completely healed or
infected- wounds and damaged or acne skin.
If it's affixed to unclean skin or too tightly, rt may
cause rashes. At this time, it should be
reduced to stick and stick for less time.

Keep out of reach of children.

Keep Away From Children Under 3 Years Old And Pets,Out Of Direct Sunlight And Store In A Cool, Dry Place

Inactive ingredients

POLYETHYLENE TEREPHTHALATE (INTRINSIC VISCOSITY 0.40-0.70) ，POLYURETHANE-39 ，CYCLOMETHICONE